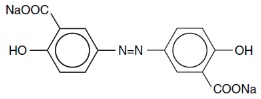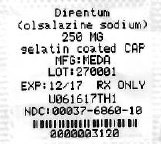 DRUG LABEL: Dipentum
NDC: 68151-0312 | Form: CAPSULE, GELATIN COATED
Manufacturer: Carilion Materials Management
Category: prescription | Type: HUMAN PRESCRIPTION DRUG LABEL
Date: 20171226

ACTIVE INGREDIENTS: OLSALAZINE SODIUM 250 mg/1 1
INACTIVE INGREDIENTS: MAGNESIUM STEARATE; FERROSOFERRIC OXIDE; CARAMEL; GELATIN, UNSPECIFIED; TITANIUM DIOXIDE

PrDipentum®
(olsalazine sodium)
capsule, gelatin coated
Rx Only
CIP70006A
PT#CIA60342
Rev. 1/2014
CIP70006A

DESCRIPTION

DESCRIPTION: The active ingredient in DIPENTUM Capsules (olsalazine sodium) is the sodium salt of a salicylate, disodium 3,3'-azobis (6-hydroxybenzoate) a compound that is effectively bioconverted to 5-aminosalicylic acid (5-ASA), which has anti-inflammatory activity in ulcerative colitis. Its empirical formula is C14H8N2Na2O6 with a molecular weight of 346.21. The structural formula is:

Olsalazine sodium is a yellow crystalline powder, which melts with decomposition at 240°C. It is the sodium salt of a weak acid, soluble in water and DMSO, and practically insoluble in ethanol, chloroform, and ether. Olsalazine sodium has acceptable stability under acidic or basic conditions.

DIPENTUM is supplied in hard gelatin capsules for oral administration. The inert ingredient in each 250 mg capsule of olsalazine sodium is magnesium stearate. The capsule shell contains the following inactive ingredients: black iron oxide, caramel, gelatin, and titanium dioxide.

CLINICAL PHARMACOLOGY

CLINICAL PHARMACOLOGY: After oral administration, olsalazine has limited systemic bioavailability. Based on oral and intravenous dosing studies, approximately 2.4% of a single 1.0 g oral dose is absorbed. Less than 1% of olsalazine is recovered in the urine. The remaining 98 to 99% of an oral dose will reach the colon, where each molecule is rapidly converted into two molecules of 5-aminosalicylic acid (5-ASA) by colonic bacteria and the low prevailing redox potential found in this environment. The liberated 5-ASA is absorbed slowly resulting in very high local concentrations in the colon.

The conversion of olsalazine to mesalamine (5-ASA) in the colon is similar to that of sulfasalazine, which is converted into sulfapyridine and mesalamine. It is thought that the mesalamine component is therapeutically active in ulcerative colitis (A.K. Azad-Kahn et al, LANCET, 2:892-895, 1977). The usual dose of sulfasalazine for maintenance of remission in patients with ulcerative colitis is 2 grams daily, which would provide approximately 0.8 gram of mesalamine to the colon. More than 0.9 gram of mesalamine would usually be made available in the colon from 1 gram of olsalazine.

The mechanism of action of mesalamine (and sulfasalazine) is unknown, but appears to be topical rather than systemic. Mucosal production of arachidonic acid (AA) metabolites, both through the cyclooxygenase pathways (i.e., prostanoids) and through the lipoxygenase pathways (i.e., leukotrienes [LTs] and hydroxyeicosatetraenoic acids [HETEs]) is increased in patients with chronic inflammatory bowel disease, and it is possible that mesalamine diminishes inflammation by blocking cyclooxygenase and inhibiting prostaglandin (PG) production in the colon.

PHARMACOKINETICS

Pharmacokinetics: The pharmacokinetics of olsalazine are similar in both healthy volunteers and in patients with ulcerative colitis. Maximum serum concentrations of olsalazine appear after approximately 1 hour and, even after a 1.0 g single dose, are low (e.g., 1.6 to 6.2 µmol/L). Olsalazine has a very short serum half-life, approximately 0.9 hour. Olsalazine is more than 99% bound to plasma proteins. It does not interfere with protein binding of warfarin. The urinary recovery of olsalazine is below 1%. Total recovery of oral ^14C-labeled olsalazine in animals and humans ranges from 90 to 97%. Approximately 0.1 % of an oral dose of olsalazine is metabolized in the liver to olsalazine-O-sulfate (olsalazine-S). Olsalazine-S, in contrast to olsalazine has a half-life of 7 days. Olsalazine-S accumulates to steady state within 2 to 3 weeks.

Patients on daily doses of 1.0 g olsalazine for 2 to 4 years show a stable plasma concentration of olsalazine-S (3.3 to 12.4 µmol/L). Olsalazine-S is more than 99% bound to plasma proteins. Its long half-life is mainly due to slow dissociation from the protein binding site. Less than 1% of both olsalazine and olsalazine-S appears undissociated in plasma.

5-aminosalicylic acid (5-ASA): Serum concentrations of 5-ASA are detected after 4 to 8 hours. The peak levels of 5-ASA after an oral dose of 1.0 g olsalazine are low (i.e., 0 to 4.3 µmol/L). Of the total 5-ASA found in the urine, more than 90% is in the form of N-acetyl-5-ASA (Ac-5-ASA). Only small amounts of 5-ASA are detected.

N-acetyl-5-ASA (Ac-5-ASA), the major metabolite of 5-ASA found in plasma and urine, is acetylated (deactivated) in at least two sites, the colonic epithelium and the liver. Ac-5-ASA is found in the serum, with peak values of 1.7 to 8.7 µmol/L after a single 1.0 g dose. Approximately 20% of the total 5-ASA is recovered in the urine, where it is found almost exclusively as Ac-5-ASA. The remaining 5-ASA is partially acetylated and is excreted in the feces. From fecal dialysis, the concentration of 5-ASA in the colon following olsalazine has been calculated to be 18 to 49 mmol/L. No accumulation of 5-ASA or Ac-5-ASA in plasma has been detected. 5-ASA and Ac-5-ASA are 74 and 81%, respectively, bound to plasma proteins.

ANIMAL PHARMACOLOGY AND OR TOXICOLOGY

ANIMAL TOXICOLOGY: Preclinical subacute and chronic toxicity studies in rats have shown the kidney to be the major target organ of olsalazine toxicity. At an oral daily dose of 400 mg/kg or higher, olsalazine treatment produced nephritis and tubular necrosis in a 4-week study; interstitial nephritis and tubular calcinosis in a 6-month study, and renal fibrosis, mineralization, and transitional cell hyperplasia in a 1-year study.

CLINICAL STUDIES

CLINICAL STUDIES: Two controlled studies have demonstrated the efficacy of olsalazine as maintenance therapy in patients with ulcerative colitis. In the first, ulcerative colitis patients in remission were randomized to olsalazine 500 mg B.I.D. or placebo, and relapse rates for a six month period of time were compared. For the 52 patients randomized to olsalazine, 12 relapses occurred, while for the 49 placebo patients, 22 relapses occurred. This difference in relapse rates was significant (p<0.02).

In the second study, 164 ulcerative colitis patients in remission were randomized to olsalazine 500 mg B.I.D. or sulfasalazine 1 gram B.I.D., and relapse rates were compared after six months. The relapse rate for olsalazine was 19.5% while that for sulfasalazine was 12.2%, a non-significant difference.

INDICATIONS AND USAGE: Olsalazine is indicated for the maintenance of remission of ulcerative colitis in patients who are intolerant of sulfasalazine.

CONTRAINDICATIONS

CONTRAINDICATIONS: Hypersensitivity to olsalazine, other salicylates, or any of the excipients.

PRECAUTIONS

GENERAL PRECAUTIONS

PRECAUTIONS: General: Overall, approximately 17% of subjects receiving olsalazine in clinical studies reported diarrhea sometime during therapy. This diarrhea resulted in withdrawal of treatment in 6% of patients. This diarrhea appears to be dose related, although it may be difficult to distinguish from the underlying symptoms of the disease.

Exacerbation of the symptoms of colitis thought to have been caused by mesalamine or sulfasalazine has been noted.

PATIENT COUNSELING INFORMATION

Information for Patients: Patients should be instructed to take olsalazine with food. The drug should be taken in evenly divided doses. Patients should be informed that about 17% of subjects receiving olsalazine during clinical studies reported diarrhea sometime during therapy. If diarrhea occurs, patients should contact their physician.

DRUG INTERACTIONS

Drug Interactions: The co-administration of salicylates and low molecular weight heparins or heparinoids may result in an increased risk of bleeding (i.e., hematomas) following neuraxial anesthesia. Salicylates should be discontinued prior to the initiation of a low molecular weight heparin or heparinoid. If this is not possible, it is recommended to monitor patients closely for bleeding.

Increased prothrombin time in patients taking concomitant warfarin has been reported.

The co-administration of olsalazine and 6-mercaptopurine or thioguanine may result in an increased risk of myelosuppression. If co-administered with 6-mercaptopurine, it is recommended to use the lowest possible doses of each drug and to monitor the patient, especially for leukopenia. In case of co-administration with thioguanine, careful monitoring of blood counts is recommended.

It is recommended not to give salicylates for six weeks after the varicella vaccine to avoid a possible increased risk of developing Reye’s syndrome.

Drug/LaboratoryTest Interactions: None known.

CARCINOGENESIS AND MUTAGENESIS AND IMPAIRMENT OF FERTILITY

Carcinogenesis, Mutagenesis, Impairment of Fertility: In a two year oral rat carcinogenicity study, olsalazine was tested in male and female Wistar rats at daily doses of 200, 400, and 800 mg/kg/day (approximately 10 to 40 times the human maintenance dose, based on a patient weight of 50 kg and a human dose of 1 g). Urinary bladder transitional cell carcinomas were found in three male rats (6%, p=0.022, exact trend test) receiving 40 times the human dose and were not found in untreated male controls. In the same study, urinary bladder transitional cell carcinoma and papilloma occurred in 2 untreated control female rats (2%). No such tumors were found in any of the female rats treated at doses up to 40 times the human dose.

In an eighteen month oral mouse carcinogenicity study, olsalazine was tested in male and female CD-1 mice at daily doses of 500, 1000, and 2000 mg/kg/day (approximately 25 to 100 times the human maintenance dose). Liver hemangiosarcomata were found in two male mice (4%) receiving olsalazine at 100 times the human dose, while no such tumor occurred in the other treated male mice groups or any of the treated female mice. The observed incidence of this tumor is within the 4% incidence in historical controls.

Olsalazine was not mutagenic in in vitro Ames tests, mouse lymphoma cell mutation assays, human lymphocyte chromosomal aberration tests, or the in vivo rat bone marrow cell chromosomal aberration test.

Olsalazine in a dose range of 100 to 400 mg/kg/day (approximately 5 to 20 times the human maintenance dose) did not influence the fertility of male or female rats. The oligospermia and infertility in men associated with sulfasalazine have not been reported with olsalazine.

PREGNANCY

TERATOGENIC EFFECTS

Pregnancy: Teratogenic Effects: Pregnancy Category C: Olsalazine has been shown to produce fetal developmental toxicity as indicated by reduced fetal weights, retarded ossifications, and immaturity of the fetal visceral organs when given during organogenesis to pregnant rats in doses 5 to 20 times the human dose (100 to 400 mg/kg).

There are no adequate and well-controlled studies in pregnant women. Olsalazine should be used during pregnancy only if the potential benefit justifies the potential risk to the fetus.

NURSING MOTHERS

Nursing Mothers: Small amounts of the active metabolite of olsalazine (5-ASA) may pass into breast milk. Harmful infant effects (diarrhea) have been reported when 5-ASA was used during breastfeeding. Unless the benefit of the treatment outweighs the risks, olsalazine should not be taken by breast-feeding women, or patients should be advised to discontinue breastfeeding if using olsalazine.

Oral administration of olsalazine to lactating rats in doses 5 to 20 times the human dose produced growth retardation in their pups.

PEDIATRIC USE

Pediatric Use: Safety and effectiveness in a pediatric population have not been established.

GERIATRIC USE

Geriatric Use: Clinical studies of DIPENTUM did not include sufficient numbers of subjects aged 65 and over to determine whether they respond differently from younger subjects. Other reported clinical experience has not identified differences in responses between the elderly and younger patients. In general, elderly patients should be treated with caution due to the greater frequency of decreased hepatic, renal, or cardiac function, co-existence of other disease, as well as concomitant drug therapy.

Severe Allergies and/or Asthma: Patients with severe allergies or asthma should be monitored for signs of worsening symptoms.

Renal: Patients with impaired renal function should be monitored.

Although renal abnormalities were not reported in clinical trials with olsalazine, there have been rare reports from post-marketing experience (see ADVERSE REACTIONS, Postmarketing). Therefore, the possibility of renal tubular damage due to absorbed mesalamine or its n-acetylated metabolite, as noted in the ANIMAL TOXICOLOGY section must be kept in mind, particularly for patients with pre-existing renal disease. In these patients, monitoring with urinalysis, BUN, and creatinine determinations is advised.

Hepatic: Patients with impaired hepatic function should be monitored (see ADVERSE REACTIONS, Postmarketing).

ADVERSE REACTIONS

To report SUSPECTED ADVERSE REACTIONS, contact Meda Pharmaceuticals Inc. at 1-888-380-3276 or FDA at 1-800-FDA-1088 or www.fda.gov/medwatch.

ADVERSE REACTIONS: Olsalazine has been evaluated in ulcerative colitis patients in remission, as well as those with acute disease. Both sulfasalazine-tolerant and intolerant patients have been studied in controlled clinical trials. Overall, 10.4% of patients discontinued olsalazine because of an adverse experience compared with 6.7% of placebo patients. The most commonly reported adverse reactions leading to treatment withdrawal were diarrhea or loose stools (olsalazine 5.9%; placebo 4.8%), abdominal pain, and rash or itching (slightly more than 1% of patients receiving olsalazine). Other adverse reactions to olsalazine leading to withdrawal occurred in fewer than 1% of patients (Table 1).

Table 1 Adverse Reactions Resulting In Withdrawal From Controlled Studies Total
 | Olsalazine (N = 441) | Placebo (N = 208)
Diarrhea/Loose Stools | 26 (5.9%) | 10 (4.8%)
Nausea | 3 | 2
Abdominal Pain | 5 (1.1%) | 0
Rash/Itching | 5 (1.1%) | 0
Headache | 3 | 0
Heartburn | 2 | 0
Rectal Bleeding | 1 | 0
Insomina | 1 | 0
Dizziness | 1 | 0
Anorexia | 1 | 0
Light Headedness | 1 | 0
Depression | 1 | 0
Miscellaneous | 4 (0.9%) | 3 (1.4%)
Total Number of Patients Withdrawn | 46 (10.4%) | 14 (6.7%)

For those controlled studies, the comparative incidences of adverse reactions reported in 1% or more patients treated with olsalazine or placebo are provided in Table 2.

Table 2 Comparative Incidence (%) of Adverse Effects Reported By One Percent Or More of Ulcerative Colitis Patients Treated With Olsalazine Or Placebo in Double Blind Controlled Studies
Adverse Event | Olsalazine (N = 441) % | Placebo (N = 208) %
Gastrointestinal Disorders
Diarrhea | 11.1 | 6.7
Abdominal Pain/Cramps | 10.1 | 7.2
Nausea | 5.0 | 3.9
Dyspepsia | 4.0 | 4.3
Bloating | 1.5 | 1.4
Vomiting | 1.0 | -
Stomatitis | 1.0 | -
Increased Blood in Stool | - | 3.4
Metabolism and Nutrition Disorders
Anorexia | 1.3 | 1.9
Nervous System Disorders
Headache | 5.0 | 4.8
Insomnia | - | 2.4
General Disorders and Administration Site Conditions
Fatigue/Drowsiness/Lethargy | 1.8 | 2.9
Psychiatric Disorders
Depression | 1.5 | -
Ear and Labyrinth Disorders
Vertigo/Dizziness | 1.0 | -
Skin and Subcutaneous Tissue Disorders
Rash | 2.3 | 1.4
Itching | 1.3 | -
Musculoskeletal and Connective Tissue Disorders
Arthralgia/Joint Pain | 4.0 | 2.9
Infections and Infestations
Upper Respiratory Infection | 1.5 | -

Over 2,500 patients have been treated with olsalazine in various controlled and uncontrolled clinical studies. In these as well as in post-marketing experience, olsalazine was administered mainly to patients intolerant to sulfasalazine. There have been rare reports of the following adverse effects in patients receiving olsalazine. These were often difficult to distinguish from possible symptoms of the underlying disease or from the effects of prior and/or concomitant therapy. A causal relationship to the drug has not been demonstrated for some of these reactions.

Blood and Lymphatic System Disorders: Anemia, Eosinophilia, Hemolytic anemia, Interstitial pulmonary disease, Leukopenia, Lymphopenia, Neutropenia, Reticulocytosis, Thrombocytopenia

Cardiac Disorders: Chest pains, Heart block second degree, Myocarditis, Palpitations, Pericarditis, Peripheral edema, Shortness of breath, Tachycardia

A patient who developed thyroid disease 9 days after starting DIPENTUM was given propranolol and radioactive iodine and subsequently developed shortness of breath and nausea. The patient died 5 days later with signs and symptoms of acute diffuse myocarditis.

Ear and Labyrinth Disorders: Tinnitus

Eye Disorders: Dry eyes, Vision blurred, Watery eyes

Gastrointestinal Disorders: Abdominal pain (upper), Diarrhea with dehydration, Dry mouth, Epigastric discomfort, Flare in symptoms, Flatulence, Increased blood in stool, Pancreatitis, Rectal bleeding, Rectal discomfort

In a double-blind, placebo-controlled study, increased frequency and severity of diarrhea were reported in patients randomized to olsalazine 500 mg B.I.D. with concomitant pelvic radiation.

Rare cases of granulomatous hepatitis and nonspecific, reactive hepatitis have been reported in patients receiving olsalazine. Additionally, a patient developed mild cholestatic hepatitis during treatment with sulfasalazine and experienced the same symptoms two weeks later after the treatment was changed to olsalazine. Withdrawal of olsalazine led to complete recovery in these cases.

General Disorders and Administration Site Conditions: Fever chills, Hot flashes, Irritability, Rigors

Immune System Disorders: Bronchospasm, Erythema nodosum

Laboratory: ALT (SGPT) or AST (SGOT) elevated beyond the normal range.

Musculoskeletal and Connective Tissue Disorders: Muscle cramps

Nervous System Disorders: Insomnia, Paraesthesia, Tremors

Psychiatric Disorders: Mood swings

Renal and Urinary Disorders: Dysuria, Hematuria, Interstitial nephritis, Nephrotic syndrome, Proteinuria, Urinary frequency

Reproductive System and Breast Disorders: Impotence, Menorrhagia

Skin and Subcutaneous Tissue Disorders: Alopecia, Erythema, Photosensitivity reaction

Vascular Disorders: Hypertension, Orthostatic hypotension

Postmarketing

The following events have been identified during post-approval use of products that contain (or are metabolized to) mesalamine in clinical practice. Because they are reported voluntarily from a population of unknown size, estimates of frequency cannot be made. These events have been chosen for inclusion due to a combination of seriousness, frequency of reporting, or potential causal connection to mesalamine:

Blood and Lymphatic System Disorders: Aplastic anemia, Pancytopenia

General Disorders and Administration Site Conditions: Pyrexia

Hepatobiliary Disorders: Hepatic enzyme increased, Hepatitis, Increased bilirubin

Reports of hepatotoxicity, including elevated liver function tests (SGOT/AST, SGPT/ALT, GGT, LDH, alkaline phosphatase, bilirubin), jaundice, cholestatic jaundice, cirrhosis, and possible hepatocellular damage including liver necrosis and liver failure. Some of these cases were fatal. One case of Kawasaki-like syndrome, which included hepatic function changes, was also reported.

Musculoskeletal and Connective Tissue Disorders: Myalgia

Respiratory, Thoracic and Mediastinal Disorders: Dyspnoea, Interstitial lung disease

Skin and Subcutaneous Tissue Disorders: Angioneurotic oedema

Nervous System Disorders: Paraesthesia, Peripheral neuropathy

Renal and Urinary Disorders: Interstitial nephritis

DRUG ABUSE AND DEPENDENCE

DRUG ABUSE AND DEPENDENCY: Abuse: None reported.

DRUG ABUSE AND DEPENDENCE

Dependence: Drug dependence has not been reported with chronic administration of olsalazine.

OVERDOSAGE

OVERDOSAGE: No overdosage has been reported in humans. The knowledge of overdosage is limited. Possible overdose symptoms include nausea, vomiting and diarrhea. It is recommended to check hematology, acid-base, electrolyte, liver and kidney status, and to provide supportive treatment. There is no specific antidote to DIPENTUM.

Maximum single oral doses of 5 g/kg in mice and rats and 2 g/kg in dogs were not lethal. Symptoms of acute toxicity were decreased motor activity and diarrhea in all species tested. In addition, vomiting was reported in dogs.

DOSAGE AND ADMINISTRATION: The usual dosage in adults for maintenance of remission is 1.0 g/day in two divided doses.

HOW SUPPLIED

Product: 68151-0312

NDC: 68151-0312-1 1 CAPSULE, GELATIN COATED in a BLISTER PACK